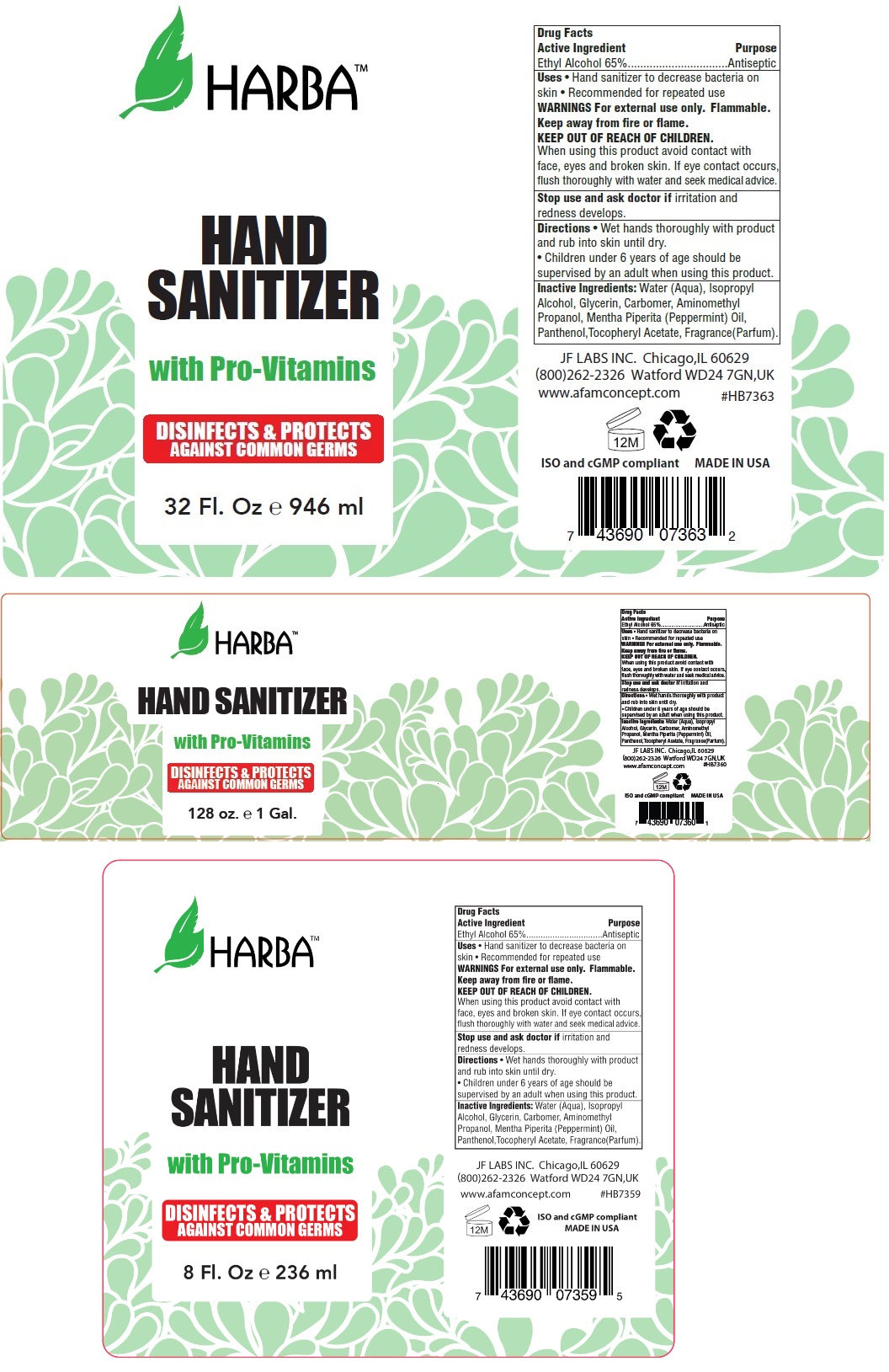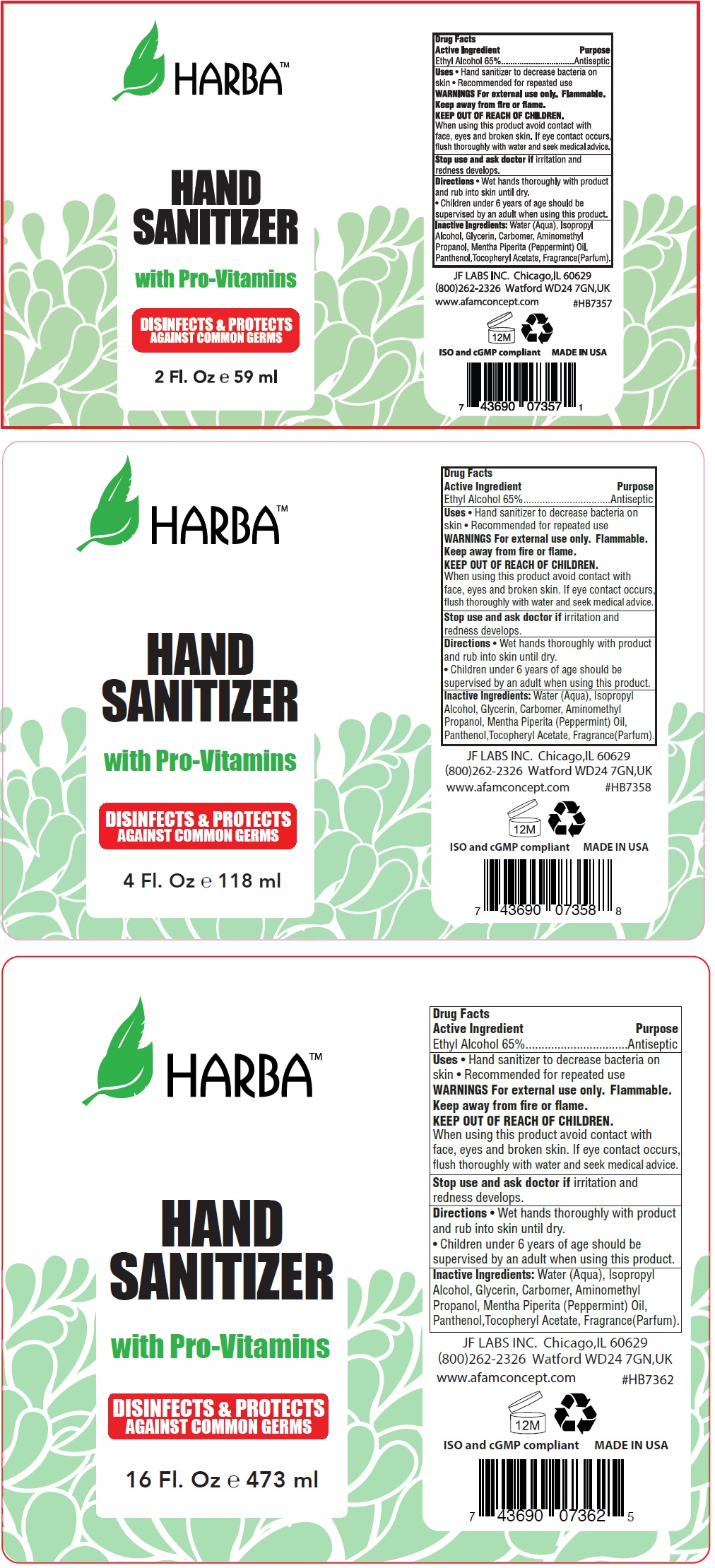 DRUG LABEL: Harba Hand Sanitizer
NDC: 49681-300 | Form: LIQUID
Manufacturer: New Life Products, Inc.
Category: otc | Type: HUMAN OTC DRUG LABEL
Date: 20210126

ACTIVE INGREDIENTS: ALCOHOL 65 mL/100 mL
INACTIVE INGREDIENTS: WATER; ISOPROPYL ALCOHOL; GLYCERIN; CARBOMER HOMOPOLYMER, UNSPECIFIED TYPE; AMINOMETHYLPROPANOL; PEPPERMINT OIL; PANTHENOL; .ALPHA.-TOCOPHEROL ACETATE

HARBA HAND SANITIZER

Active Ingredient

Ethyl Alcohol 65%

Purpose

Antiseptic

Uses

• Hand sanitizer to decrease bacteria on skin

• Recommended for repeated use

WARNINGS

For external use only. Flammable.

Keep away from fire or flame.

When using this product avoid contact with face, eyes and broken skin. If eye contact occurs,

flush thoroughly with water and seek medical advice.

Stop use and ask a doctor if irritation and redness develops.

KEEP OUT OF REACH OF CHILDREN

Directions

• Wet hands thoroughly with product and rub into skin until dry.

• Children under 6 years of age should be supervised by an adult when using this product

Inactive Ingredients:

Water (Aqua), Isopropyl Alcohol, Glycerin, Carbomer, Aminomethyl Propanol, Mentha Piperita (Peppermint) Oil, Panthenol, Tocopheryl Acetate, Fragrance(Parfum).

With Pro-Vitamins

DISINFECTANTS & PROTECTS AGAINST COMMON GERMS

JF LABS INC. Chicago,IL 60629

(800)262-2326 Watford WD247GN, UK

www.afamconcept.com

ISO and cGMP compliant

MADE IN USA